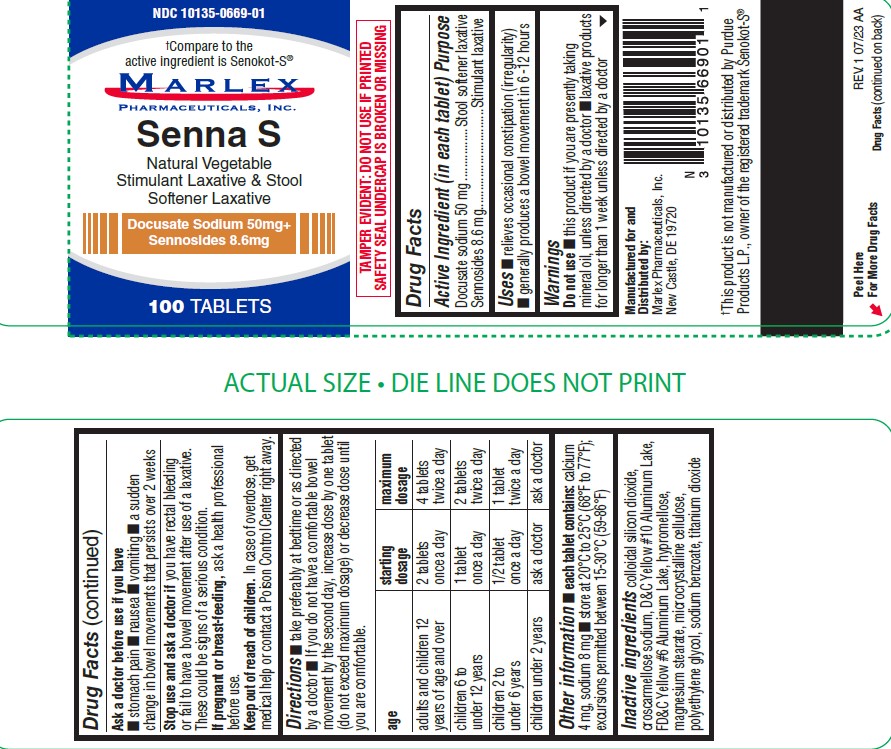 DRUG LABEL: Senna S
NDC: 10135-669 | Form: TABLET
Manufacturer: Marlex Pharmaceuticals Inc
Category: otc | Type: HUMAN OTC DRUG LABEL
Date: 20251121

ACTIVE INGREDIENTS: SENNOSIDES 8.6 mg/1 1; DOCUSATE SODIUM 50 mg/1 1
INACTIVE INGREDIENTS: SILICON DIOXIDE; CROSCARMELLOSE SODIUM; D&C YELLOW NO. 10; FD&C YELLOW NO. 6; HYPROMELLOSES; MAGNESIUM STEARATE; CELLULOSE, MICROCRYSTALLINE; POLYETHYLENE GLYCOL, UNSPECIFIED; SODIUM BENZOATE; TITANIUM DIOXIDE

Senna S

SENNOSIDES AND DOCUSATE SODIUM-sennosides, docusate sodium tablet Marlex Pharmaceuticals, Inc.

Disclaimer: Most OTC drugs are not reviewed and approved by FDA, however they may be marketed if they comply with applicable regulations and policies. FDA has not evaluated whether this product complies.

----------

Senna S

Drug Facts

Active ingredient (in each tablet)

Docusate Sodium 50mg Sennosides 8.6 mg

Purpose

Stool softener Stimulant laxative

Uses

- relieves occasional constipation (irregularity)
- generally causes bowel movement in 6-12 hours

Warnings

Do not use

- this product if you are presently taking mineral oil, unless directed by a doctor
- laxative products for longer than 1 week unless directed by a doctor

Ask a doctor before use if you have

- stomach pain
- Nausea
- Vomiting
- a sudden change in bowel movements that persists over 2 weeks

Stop use and ask a doctorif

you have rectal bleeding or fail to have a bowel movement after use if a laxative. These could be signs of a serious condition.

If pregnant or breast-feeding,

ask a health professional before use.

Keep out of reach of children.

In case of overdose, get medical help or contact a Poison Control Center right away.

Directions

- take preferably at bedtime or as directed by a doctor
- if you do not have a comfortable bowel movement by the second day, increase does by one tablet (do not exceed maximum dosage) or decrease does until you are comfortable

age | starting dosage | maximum dosage
adults and children 12 years of age and older | 2 tablets once a day | 4 tablets twice a day
children 6 to 12 years | 1 tablet once a day | 2 tablets twice a day
children 2 to 6 years | 1/2 tablet once a day | 1 tablet twice a day
children under 2 years | ask a doctor | ask a doctor

Other information

- each tablet contains:calcium 4mg, sodium 8mg
- store at 20°C to 25°C (68°F to 77°F) excursions permitted between 15°30°C (59°-86°F)

Inactive ingredients

Colloidal silicon dioxide, croscarmellose sodium, D&C Yellow #10 Aluminum Lake, FD&C Yellow #6 Aluminum Lake, hypromellose, magnesium stearate, microcrystalline cellulose, polyethylene glycol, sodium benzoate, titanium dioxide

*Compare to the active ingredients in SENOKOT-S®

PRINCIPAL DISPLAY PANEL

NDC 10135-0669-01
Senna S
100 TABLET